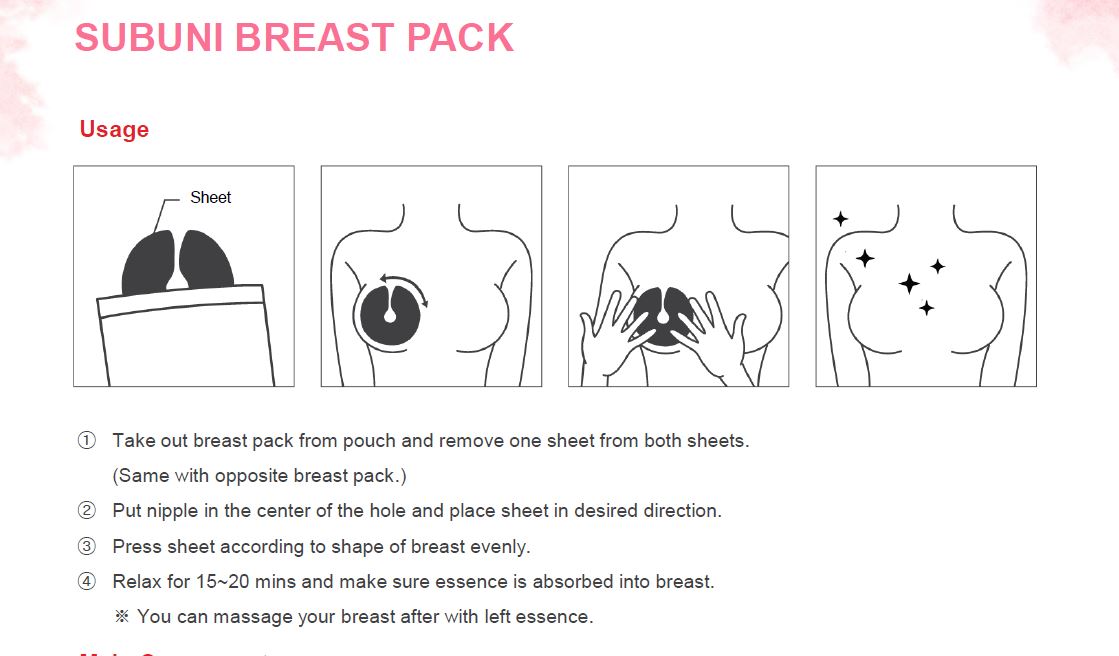 DRUG LABEL: SUBUNI BREAST PACK
NDC: 75397-0002 | Form: LIQUID
Manufacturer: MERLIN
Category: otc | Type: HUMAN OTC DRUG LABEL
Date: 20200419

ACTIVE INGREDIENTS: NIACINAMIDE 2 g/100 g; ADENOSINE 0.04 g/100 g
INACTIVE INGREDIENTS: WATER; GLYCERIN; HYALURONATE SODIUM; ALLANTOIN

ACTIVE INGREDIENT

adenosine, niacinamide

INACTIVE INGREDIENT

Water
Sorbitol
Methylpropanediol
Dipropylene Glycol
Propylene Glycol
Glycerin
Betaine
Trehalose
Sodium Hyaluronate
Phenoxyethanol
Hydroxyethylcellulose
Polysorbate 80
Anemarrhena Asphodeloides Root Extract
Punica Granatum Fruit Extract
Honey Extract
Hydrolyzed Elastin
Broussonetia Extract
Malva Sylvestris (Mallow) flower / leaf / stem extract
Mentha Piperita (Peppermint) leaf extract
Primula Veris flower extract
Alchemilla Vulgaris flower / leaf / stem extract
Veronica Officinalis flower / leaf / stem extract
Melissa Officinalis leaf extract
Achillea Millefolium flower / leaf / stem extract
Allantoin
Carbomer
Lavandula Spica (Lavender) Flower Oil
Disodium EDTA
Acetyl Hexapeptide-8

PURPOSE

wrinkle care, whitening

WARNINGS

■ if following abnormal symptoms persist, discontinue use

Irritation around the eyes, ears, mucous membranes, including the mouth, under the skin irritation and rashes

■ Stop immediately and consult a doctor if you experience

1) Hypersensitivity symptoms such as erythema, itching and dermatitis.

2) Skin Irritation

3) Following Instructions when using medication

(1) For external use only (Do not use internally)

(2) Avoid getting into the eyes (if contact occurs, wash well with clean water)

■ Be careful not to inhale or use excessively for a long time (ingesting ethanol repeatedly causes irritation to mucous membranes and headaches or other symptoms may appear. When used repeatedly in the same area, skin irritation may occur.

■ Do not use the product for a long time in the same area as swelling, inflammation or sickness may occur due to absorption through the skin.

It is not recommended to use this one areas that have been medically treated with a cast or bandage.

■ Do not use in combination with soap or antibacterial cleansing agents.

• Keep Out of Reach of Children.

INDICATIONS AND USAGE

①Take out breast pack from pouch and remove one sheet from both sheets. (Same with opposite breast pack.)
②Put nipple in the center of the hole and place sheet in desired direction.
③Press sheet according to shape of breast evenly.
④Relax for 15~20 mins and make sure essence is absorbed into breast. ※ You can massage your breast after with left essence.

DOSAGE AND ADMINISTRATION

for external use only